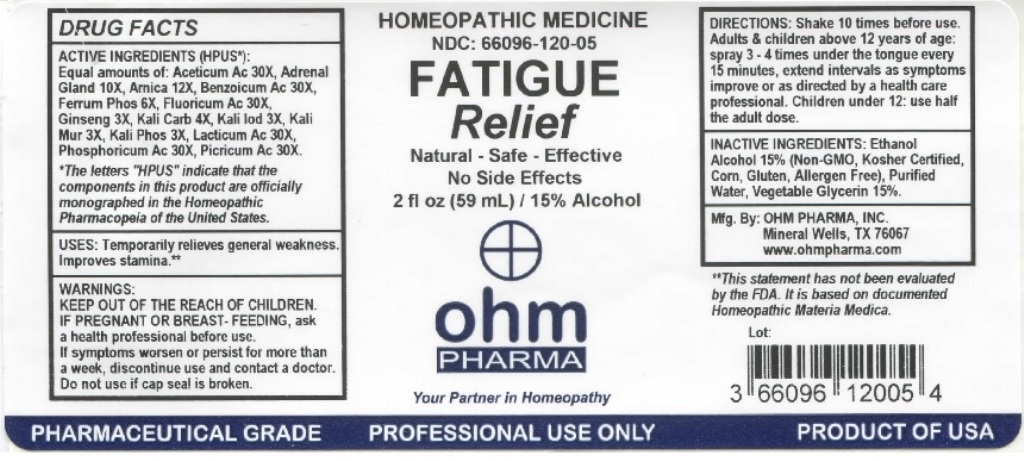 DRUG LABEL: OHM Fatigue Relief
NDC: 66096-120 | Form: LIQUID
Manufacturer: OHM PHARMA INC.
Category: homeopathic | Type: HUMAN OTC DRUG LABEL
Date: 20211229

ACTIVE INGREDIENTS: ACETIC ACID 30 [hp_X]/59 mL; BOS TAURUS ADRENAL GLAND 10 [hp_X]/59 mL; ARNICA MONTANA 12 [hp_X]/59 mL; BENZOIC ACID 30 [hp_X]/59 mL; FERROSOFERRIC PHOSPHATE 6 [hp_X]/59 mL; HYDROFLUORIC ACID 30 [hp_X]/59 mL; ASIAN GINSENG 3 [hp_X]/59 mL; POTASSIUM CARBONATE 4 [hp_X]/59 mL; POTASSIUM IODIDE 3 [hp_X]/59 mL; POTASSIUM CHLORIDE 3 [hp_X]/59 mL; DIBASIC POTASSIUM PHOSPHATE 3 [hp_X]/59 mL; LACTIC ACID, DL- 30 [hp_X]/59 mL; PHOSPHORIC ACID 30 [hp_X]/59 mL; PICRIC ACID 30 [hp_X]/59 mL
INACTIVE INGREDIENTS: ALCOHOL; WATER; GLYCERIN

OHM Fatigue Relief

ACTIVE INGREDIENT

ACTIVE INGREDIENTS (HPUS*): Equal amounts of: Aceticum Ac 30X, Adrenal Gland 10X, Arnica 12X, Benzoicum Ac 30X, Ferrum Phos 6X, Fluoricum Ac 30X, Ginseng 3X, Kali Carb 4X, Kali lod 3X, Kali Mur 3X, Kali Phos 3X, Lacticum Ac 30X, Phosphoricum Ac 30X, Picricum Ac 30X.

*The letters "HPUS" indicate that the components in this product are officially mongraphed in the Homeopathic Pharmacopeia of the United States.

INDICATIONS AND USAGE

USES: Temporarily relieves general weakness. Improves stamina.**

**This statement has not been evaluated by the FDA. It is based on documented Homeopathic Materia Medica.

WARNINGS

IF PREGNANT OR BREAST-FEEDING, ask a health professional before use. If symptoms worsen or persist for more than a week, discontinue use and contact a doctor.

- KEEP OUT OF REACH OF CHILDREN.

DOSAGE AND ADMINISTRATION

DIRECTIONS: Shake 10 times before use. Adults & children above 12 years of age: spray 3-4 times under the tongue every 15 minutes, extend intervals as symptoms improve or as directed by a health care professional. Children under 12: use half the adult dose.

Do not use if cap seal is broken.

INACTIVE INGREDIENT

INACTIVE INGREDIENTS: Ethanol Alcohol 15% (Non-GMO, Kosher Certified, Corn, Gluten, Allergen Free). Purified Water, Vegetable Glycerin 15%.

QUESTIONS

Mfg. By: OHM PHARMA, INC. Mineral Wells, TX 76067

www.ohmpharma.com

PACKAGE LABEL

HOMEOPATHIC MEDICINE

NDC: 66096-120-05

FATIGUE Relief

Natural - Safe - Effective

No Side Effects

2 fl oz (59mL) / 15% Alcohol

PRODUCT OF USA

PURPOSE

Temporarily relieves general weakness.